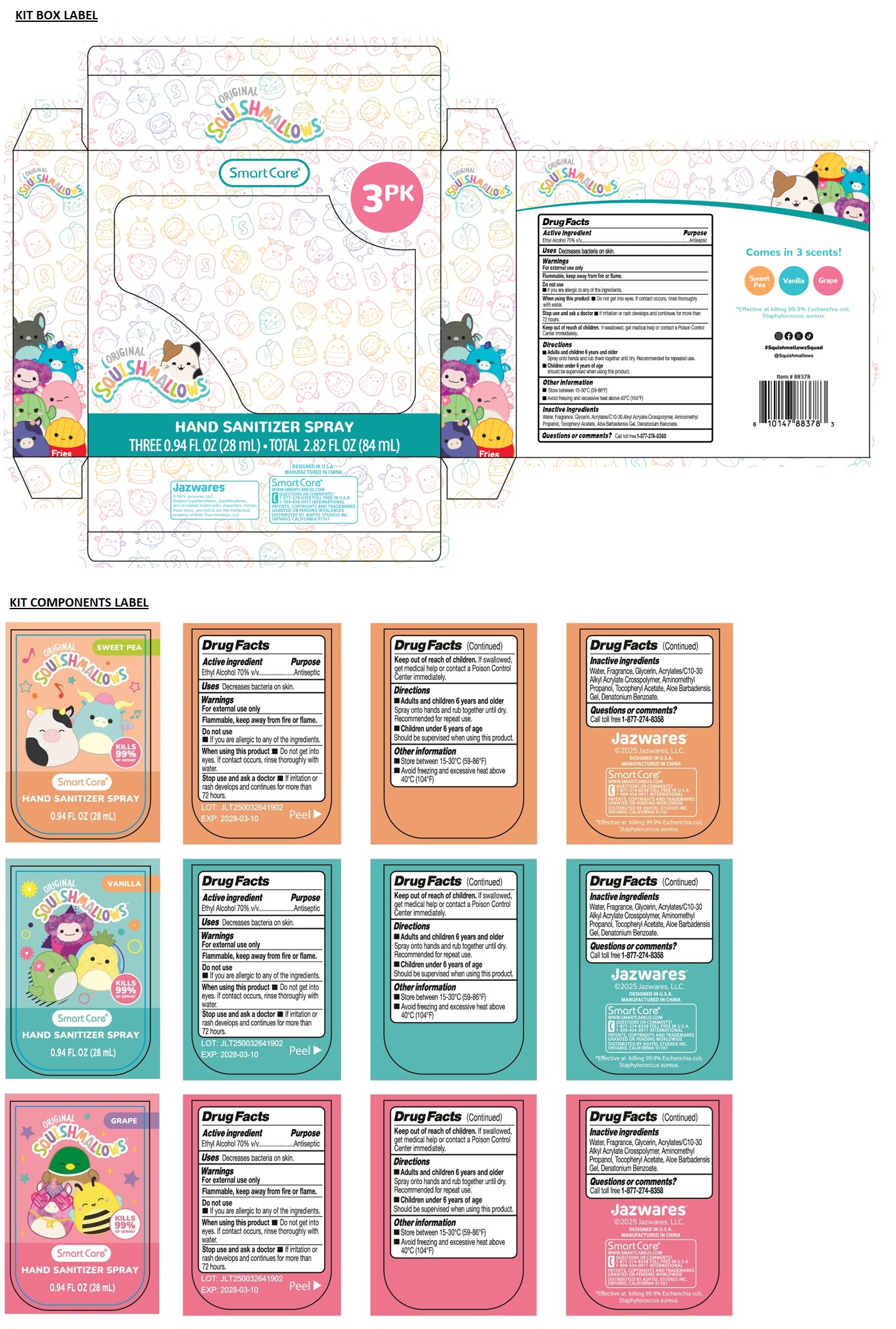 DRUG LABEL: Smart Care HAND SANITIZER 0.94 FL OZ 3PK - SQUISHMALLOWS
NDC: 70108-136 | Form: KIT | Route: TOPICAL
Manufacturer: Ashtel Studios, Inc.
Category: otc | Type: HUMAN OTC DRUG LABEL
Date: 20250409

ACTIVE INGREDIENTS: ALCOHOL 70 mL/100 mL; ALCOHOL 70 mL/100 mL; ALCOHOL 70 mL/100 mL
INACTIVE INGREDIENTS: WATER; GLYCERIN; ACRYLATES/C10-30 ALKYL ACRYLATE CROSSPOLYMER (60000 MPA.S); AMINOMETHYLPROPANOL; .ALPHA.-TOCOPHEROL ACETATE; ALOE VERA LEAF; DENATONIUM BENZOATE; WATER; GLYCERIN; ACRYLATES/C10-30 ALKYL ACRYLATE CROSSPOLYMER (60000 MPA.S); AMINOMETHYLPROPANOL; .ALPHA.-TOCOPHEROL ACETATE; ALOE VERA LEAF; DENATONIUM BENZOATE; WATER; GLYCERIN; ACRYLATES/C10-30 ALKYL ACRYLATE CROSSPOLYMER (60000 MPA.S); AMINOMETHYLPROPANOL; .ALPHA.-TOCOPHEROL ACETATE; ALOE VERA LEAF; DENATONIUM BENZOATE

Smart Care® 3 PK SQUISHMALLOWS HAND SANITIZER SPRAY

Active ingredient

Ethyl Alcohol 70% v/v

Purpose

Antiseptic

Uses

Decreases bacteria on skin.

Warnings

For external use only

Flammable, keep away from fire or flame.

Do not use
• If you are allergic to any of the ingredients.

When using this product • Do not get into eyes. If contact occurs, rinse thoroughly with water.

Stop use and ask a doctor • If irritation or rash develops and continues for more than 72 hours.

Keep out of reach of children. If swallowed, get medical help or contact a Poison Control Center immediately.

Directions

• Adults and children 6 years and older
Spray onto hands and rub them together until dry. Recommended for repeated use.

• Children under 6 years of age
should be supervised when using this product.

Other information

• Store between 15-30°C (59-86°F)
• Avoid freezing and excessive heat above 40°C (104°F)

Inactive ingredients

Water, Fragrance, Glycerin, Acrylates/C10-30 Alkyl Acrylate Crosspolymer, Aminomethyl Propanol, Tocopheryl Acetate, Aloe Barbadensis Gel, Denatonium Benzoate.

Questions or comments?

Call toll free 1-877-274-8358

ORIGINAL

Comes in 3 scents!

Sweet Pea

Vanilla

Grape

*Effective at killing 99.9% Escherichia coli, Staphylococcus aureus.

#SquishmallowsSquad

@Squishmallows

Jazwares™
©2025 Jazwares, LLC.
Original Squishmallows, Squishmallows, and all related trademarks, characters, names, trade dress, and indicia are the intellectural property of Kelly Toys Holdings, LLC.

DESIGNED IN U.S.A.

MANUFACTURED IN CHINA

SmartCare®

WWW.SMARTCARE.US.COM
1-909-434-0911 INTERNATIONAL

PATENTS, COPYRIGHTS AND TRADEMARKS GRANTED OR PENDING WORLDWIDE

DISTRIBUTED BY ASHTEL STUDIOS INC.
ONTARIO, CALIFORNIA 91761